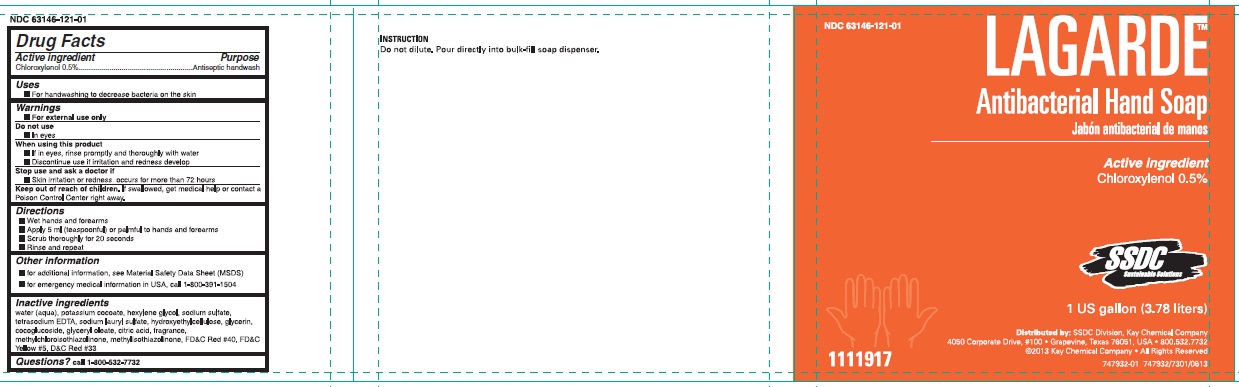 DRUG LABEL: Lagarde
NDC: 47593-675 | Form: SOLUTION
Manufacturer: Ecolab Inc.
Category: otc | Type: HUMAN OTC DRUG LABEL
Date: 20251230

ACTIVE INGREDIENTS: CHLOROXYLENOL 0.5 mg/100 mL
INACTIVE INGREDIENTS: WATER; POTASSIUM COCOATE; HEXYLENE GLYCOL; SODIUM SULFATE ANHYDROUS; EDETATE SODIUM; SODIUM LAURYL SULFATE; HYDROXYETHYL CELLULOSE (3000 MPA.S AT 1%); GLYCERIN; COCO-GLUCOSIDE; GLYCERYL OLEATE; ANHYDROUS CITRIC ACID; METHYLCHLOROISOTHIAZOLINONE; METHYLISOTHIAZOLINONE; FD&C RED NO. 40; FD&C YELLOW NO. 5; D&C RED NO. 33

Drug Facts

Active ingredient

Chloroxylenol 0.5%

Purpose

Antiseptic handwash

Uses

- For handwashing to decrease bacteria on the skin

Warnings

- For external use only

Do not use

- In eyes

When using this product

- If in eyes, rinse promptly and thoroughly with water
- Discontinue use if irritation and redness develop

Stop use and ask a doctor if

- Skin irritation or redness occurs for more than 72 hours

Keep out of reach of children. If swallowed, get medical help or contact a Poison Control Center right away.

Directions

- Wet hands and forearms
- Apply 5 ml (teaspoonful) or palmful to hands and forearms
- Scrub throughly for 20 seconds
- Rinse and repeat

Other information

- for additional information, see Material Safety Data Sheet (MSDS)
- for emergency medical information in USA, call 1-800-391-1504

Inactive ingredients

water (aqua), potassium cocoate, hexylene glycol, sodium sulfate, tetrasodium EDTA, sodium lauryl sulfate, hydroxyethylcellulose, glycerin, cocoglucoside, glyceryl oleate, citric acid, fragrance, methylchloroisothiazolinone, methylisothiazolinone, FD&C Red #40, FD&C Yellow #5, D&C Red #33

Principal display panel and representative label

NDC 63149-121-01

LAGARDE™

Antibacterial Hand Soap

Active ingredient

Chloroxylenol 0.5%

SSDC Sustainable Solutions

1 US gallon (3.78 liters)

Distributed by: SSDC Division, Kay Chemical Company

4050 Corporate Drive, #100 • Grapevine, Texas 76051, USA • 800.532.7732

©2013 Kay Chemical Company • All Rights Resevrved

1111917

747932-01 747932/7300/0613